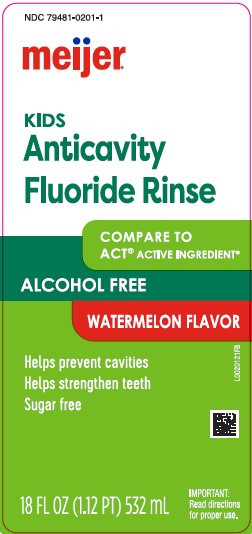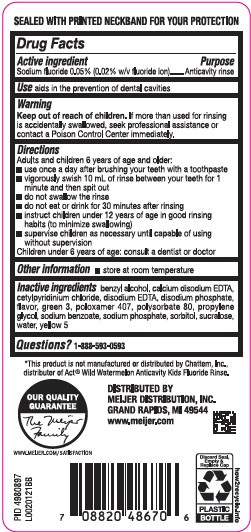 DRUG LABEL: Anticavity Rinse
NDC: 79481-0201 | Form: MOUTHWASH
Manufacturer: Meijer, Inc.
Category: otc | Type: HUMAN OTC DRUG LABEL
Date: 20260219

ACTIVE INGREDIENTS: SODIUM FLUORIDE 0.2 mg/1 mL
INACTIVE INGREDIENTS: BENZYL ALCOHOL; EDETATE CALCIUM DISODIUM; CETYLPYRIDINIUM CHLORIDE; EDETATE DISODIUM; MEPREDNISONE DISODIUM PHOSPHATE; FD&C GREEN NO. 3; POLOXAMER 407; POLYSORBATE 80; PROPYLENE GLYCOL; SODIUM BENZOATE; SODIUM PHOSPHATE; SORBITOL; SUCRALOSE; WATER; FD&C YELLOW NO. 5

Meijer 201.000/201AA
Watermelon Anticavity Mouthwash

Tamper Evident Statement

SEALED WITH PRINTED NECKBAND FOR YOUR PROTECTION

Active ingredient

Sodium fluoride 0.05% (0.02% w/v fluoride ion)

Purpose

Anticavity rinse

Use

aids in the prevention of dental cavities

Warnings

for this product

Keep out of reach of children.

If more than used for rinsing is accidentally swallowed, seek professional assistance or contact a Poison Control Center immediately.

Directions

Adults and children 6 years of age and older:

- use once a day after brushing your teeth with a toothpaste
- vigorously swish 10 milliliters of rinse between your teeth for 1 minute and then spit out
- do not swallow the rinse
- do not eat or drink for 30 minutes after rinsing
- instruct children under 12 years of age in good rinsing habits (to minimize swallowing)
- supervise children as necessary until capable of using without supervision

Children under 6 years of age: consult a dentist or doctor

Other information

Store at room temperature

Inactive ingredients

benzyl alcohol, calcium disodium EDTA, cetylpyridinium chloride, disodium EDTA, disodium phosphate, flavor, green 3, poloxamer 407, polysorbate 80, propylene glycol, sodium benzoate, sodium phosphate, sorbitol, sucralose, water, yellow 5

Questions?

1-888-593-0593

Disclaimer

*This product is not manufactured or distributed by Chattem, Inc., distributor of Act® Wild Watermelon Anticavity Kids Fluoride Rinse.

Adverse reactions

DISTRIBUTED BY

MEIJER DISTRIBUTIONS, INC.

GRAND RAPIDS, MI 49544

www.meijer.com

OUR QUALITY GUARANTEE

The Meijer Family

WWW.MEIJER.COM/SATISFACTION

Discard Seal, Empty & Replace Cap

PLASTIC BOTTLE

how2recycle.info

Principal display panel

NDC 79481-0201-1

meijer®

KIDS

Anticavity

Fluoride Rinse

Compare to ACT® ACTIVE INGREDIENT*

ALCOHOL FREE

WATERMELON FLAVOR

Helps prevent cavities

Helps strengthen teeth

Sugar free

18 FL OZ (1.12 PT) 532 mL

IMPORTANT: Read directions for proper use.